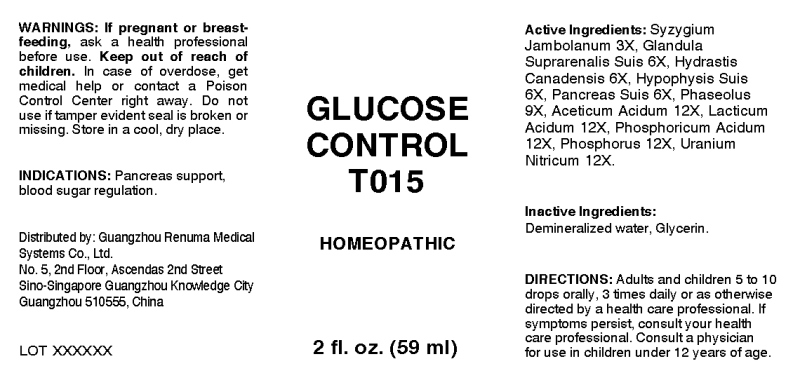 DRUG LABEL: Glucose Control
NDC: 71742-0009 | Form: LIQUID
Manufacturer: Guangzhou Renuma Medical Systems Co., Ltd
Category: homeopathic | Type: HUMAN OTC DRUG LABEL
Date: 20171026

ACTIVE INGREDIENTS: SYZYGIUM CUMINI SEED 3 [hp_X]/1 mL; SUS SCROFA ADRENAL GLAND 6 [hp_X]/1 mL; GOLDENSEAL 6 [hp_X]/1 mL; SUS SCROFA PITUITARY GLAND 6 [hp_X]/1 mL; SUS SCROFA PANCREAS 6 [hp_X]/1 mL; KIDNEY BEAN 9 [hp_X]/1 mL; ACETIC ACID 12 [hp_X]/1 mL; LACTIC ACID 12 [hp_X]/1 mL; PHOSPHORIC ACID 12 [hp_X]/1 mL; PHOSPHORUS 12 [hp_X]/1 mL; URANYL NITRATE HEXAHYDRATE 12 [hp_X]/1 mL
INACTIVE INGREDIENTS: WATER; GLYCERIN

Drug Facts:

ACTIVE INGREDIENTS:

Syzygium Jambolanum 3X, Glandula Suprarenalis Suis 6X, Hydrastis Canadensis 3X, Hypophysis Suis 6X, Pancreas Suis 6X, Phaseolus 9X, Aceticum Acidum 12X, Lacticum Acidum 12X, Phosphoricum Acidum 12X, Phosphorus 12X, Uranium Nitricum 12X.

INDICATIONS:

Pancreas support, blood sugar regulation.

WARNINGS:

If pregnant or breast-feeding, ask a health care professional before use.
Keep out of reach of children. In case of overdose, get medical help or contact a Poison Control Center right away.
Do not use if tamper evident seal is broken or missing.
Store in cool, dry place.

Keep out of reach of children. In case of overdose, get medical help or contact a Poison Control Center right away.

DIRECTIONS:

Adults and children 5 to 10 drops orally, 3 times daily or as otherwise directed by a health care professional. If symptoms persist, consult your health care professional. Consult a physician for use in children under 12 years of age.

INDICATIONS:

Pancreas support, blood sugar regulation.

INACTIVE INGREDIENTS:

Demineralized water, Glycerin

QUESTIONS:

Distributed by:
Guangzhou Renuma Medical
Systems Co., Ltd.
No. 5, 2nd Floor, Ascendas 2nd Street
Sino-Singapore Guangzhou Knowledge City
Guangzhou 510555, China

PACKAGE LABEL DISPLAY:

GLUCOSE

CONTROL

T015

HOMEOPATHIC

2 fl. oz. (59 ml)